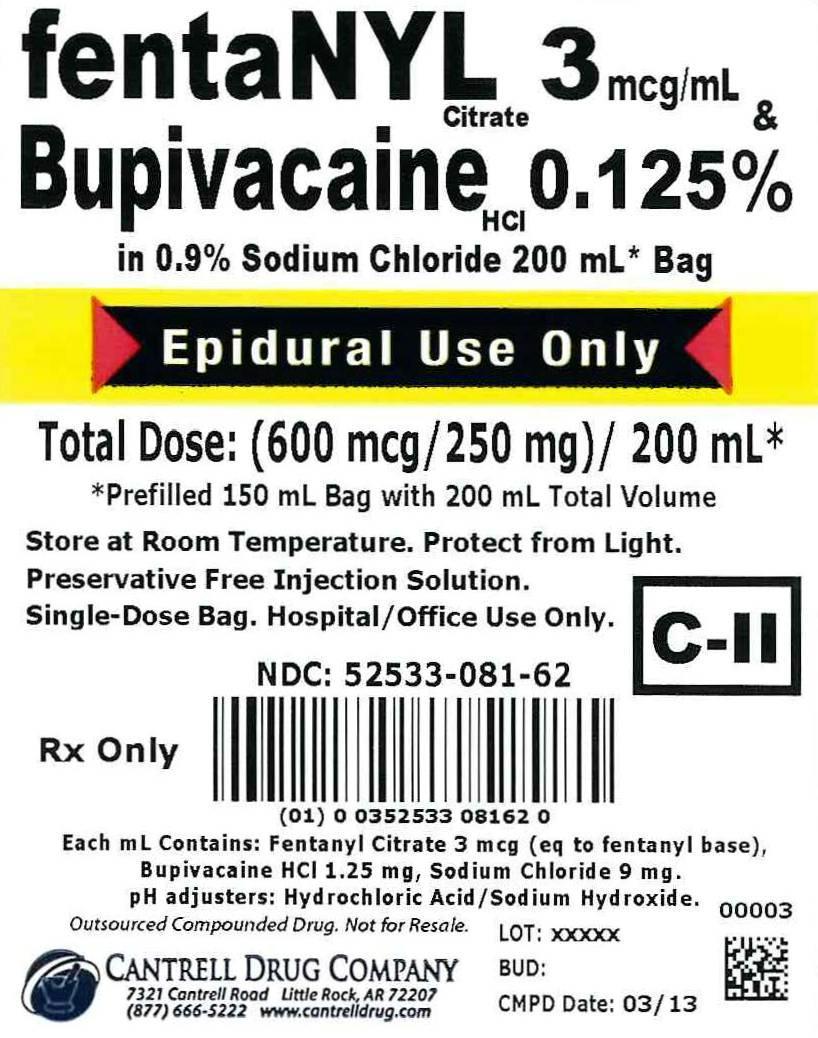 DRUG LABEL: Fentanyl Citrate, Bupivacaine HCl
NDC: 52533-081 | Form: INJECTION, SOLUTION
Manufacturer: Cantrell Drug Company
Category: prescription | Type: HUMAN PRESCRIPTION DRUG LABEL
Date: 20140812
DEA Schedule: CII

ACTIVE INGREDIENTS: Fentanyl Citrate 3 ug/1 mL; BUPIVACAINE HYDROCHLORIDE 1.25 mg/1 mL
INACTIVE INGREDIENTS: Sodium Chloride 9 mg/1 mL; Water

Fentanyl Citrate 3 mcg/mL & Bupivacaine HCl 0.125% in 0.9% Sodium Chloride 200 mL Bag